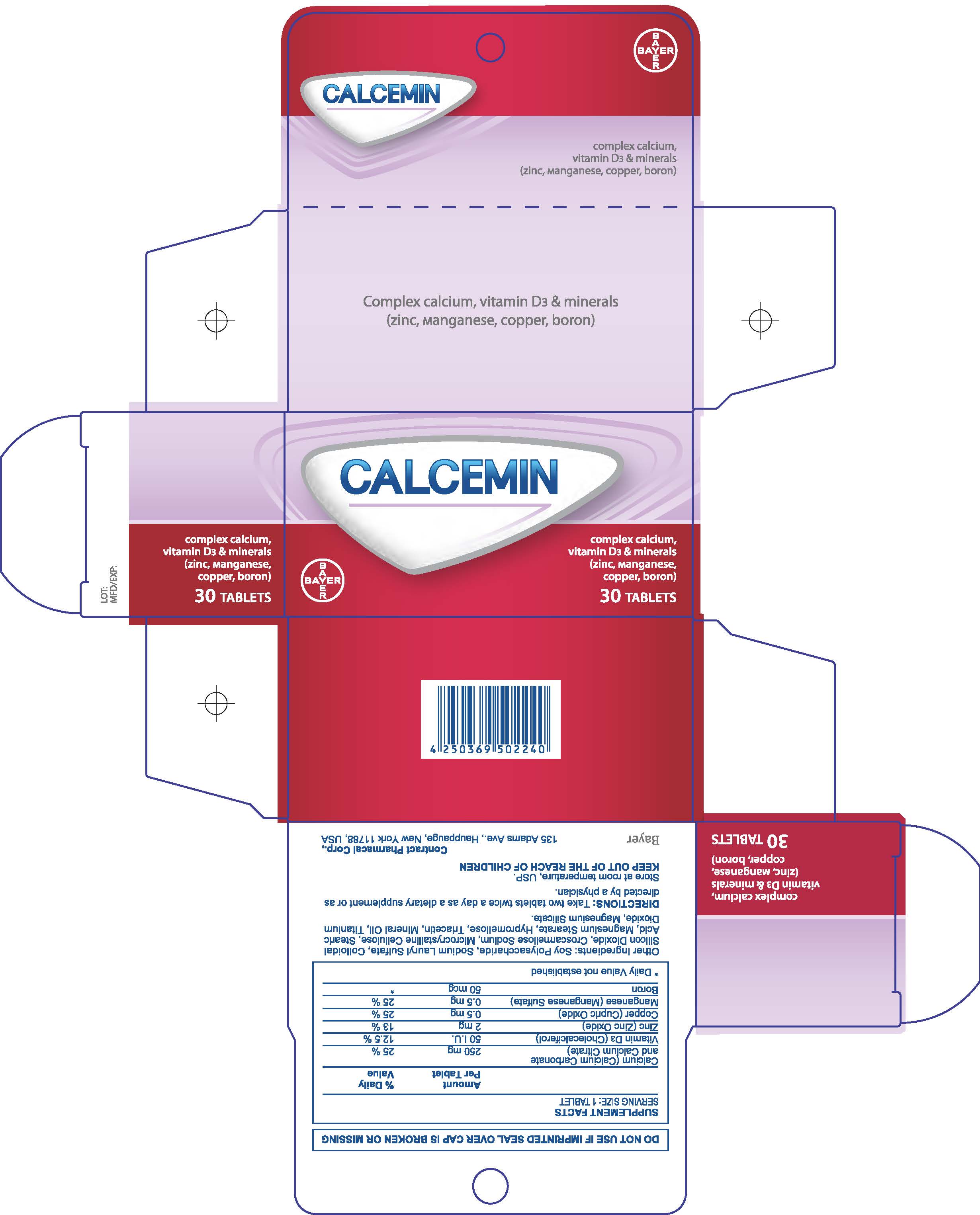 DRUG LABEL: Calcemin
NDC: 0280-0271 | Form: TABLET, FILM COATED
Manufacturer: Bayer HealthCare LLC.
Category: otc | Type: HUMAN OTC DRUG LABEL
Date: 20260108

ACTIVE INGREDIENTS: PREVITAMIN D3 0.75 mg/1 1; ZINC 2 mg/1 1; BORON 50 ug/1 1
INACTIVE INGREDIENTS: WATER; CROSCARMELLOSE SODIUM; CELLULOSE, MICROCRYSTALLINE; STEARIC ACID; MAGNESIUM STEARATE; HYPROMELLOSES; TRIACETIN; MINERAL OIL; SODIUM LAURYL SULFATE; TITANIUM DIOXIDE; MAGNESIUM SILICATE

Calcimin Tablets - Georgia

Drug Facts